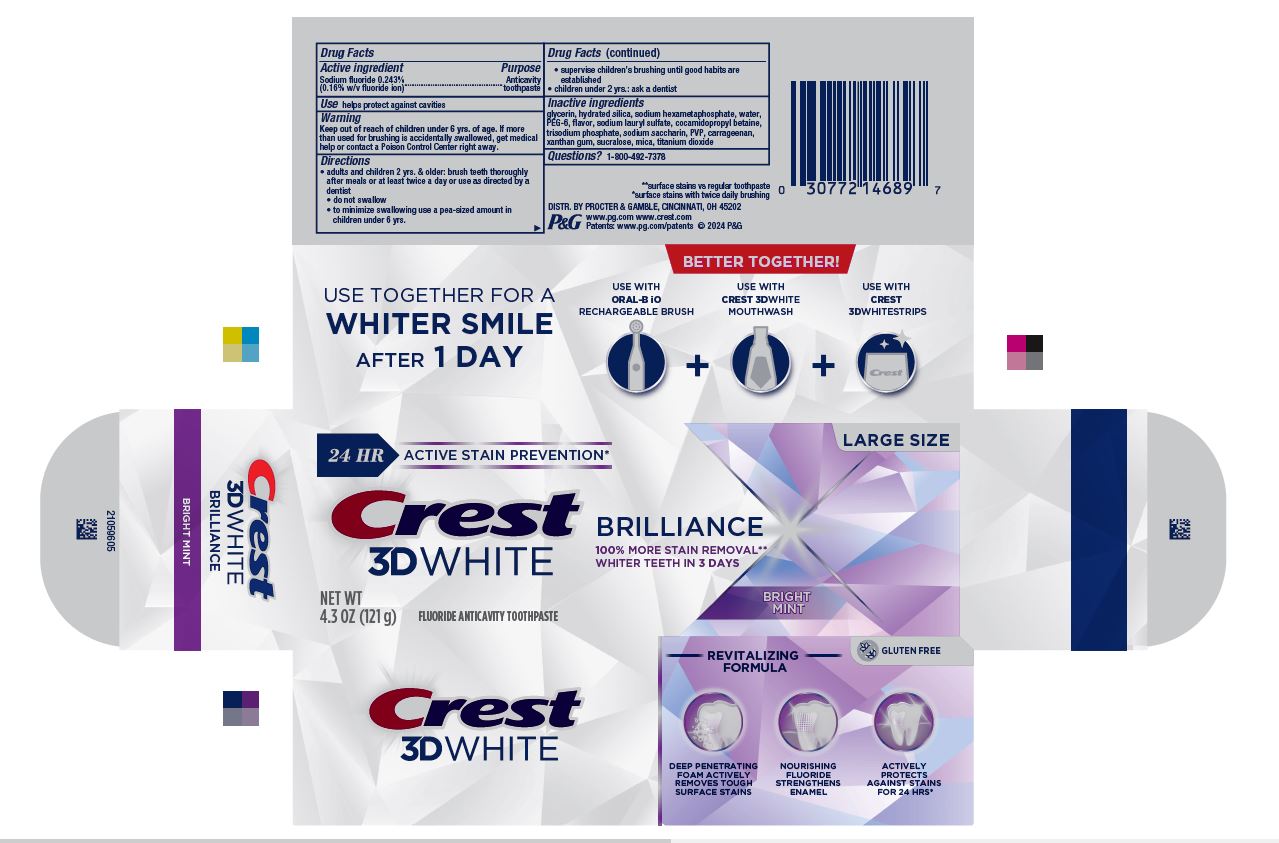 DRUG LABEL: Crest 3D White
NDC: 84126-601 | Form: PASTE, DENTIFRICE
Manufacturer: Procter & Gamble Manfuacturing Company
Category: otc | Type: HUMAN OTC DRUG LABEL
Date: 20240723

ACTIVE INGREDIENTS: SODIUM FLUORIDE 1.5 mg/1 g
INACTIVE INGREDIENTS: POLYETHYLENE GLYCOL 300; SODIUM POLYMETAPHOSPHATE; POVIDONE, UNSPECIFIED; XANTHAN GUM; SODIUM PHOSPHATE, TRIBASIC, ANHYDROUS; WATER; HYDRATED SILICA; SODIUM LAURYL SULFATE; SUCRALOSE; TITANIUM DIOXIDE; SACCHARIN SODIUM; GLYCERIN; MICA; COCAMIDOPROPYL BETAINE; CARRAGEENAN

Crest 3D White Brilliance Bright Mint

Drug Facts

Active ingredient

Sodium fluoride 0.243% (0.16% w/v fluoride ion)

Purpose

Anticavity toothpaste

Use

helps protect against cavities

Warnings

Keep out of reach of children under 6 yrs. of age.If more than used for brushing is accidentally swallowed, get medical help or contact a Poison Control Center right away.

Directions

- adults and children 2 yrs. & older: brush teeth thoroughly after meals or at least twice a day or use as directed by a dentist
  - do not swallow
  - to minimize swallowing use a pea-sized amount in children under 6
  - supervise children's brushing until good habits are established
- children under 2 yrs.: ask a dentist

Inactive ingredients

glycerin, hydrated silica, sodium hexametaphosphate, water,
PEG-6, flavor, sodium lauryl sulfate, cocamidopropyl betaine,
trisodium phosphate, sodium saccharin, PVP, carrageenan,
xanthan gum, sucralose, mica, titanium dioxide

Questions?

1-800-492-7378

DISTR. BY PROCTER & GAMBLE,

CINCINNATI, OH 45202

PRINCIPAL DISPLAY PANEL - 110 g Carton

24 HR ACTIVE STAIN PREVENTION* LARGE SIZE

Crest®

3D WHITE

FLUORIDE ANTICAVITY TOOTHPASTE

BRILLIANCE

100% MORE STAIN REMOVAL**

WHITER TEETH IN 3 DAYS

BRIGHT MINT

NET WT 4.3 OZ (121 g)